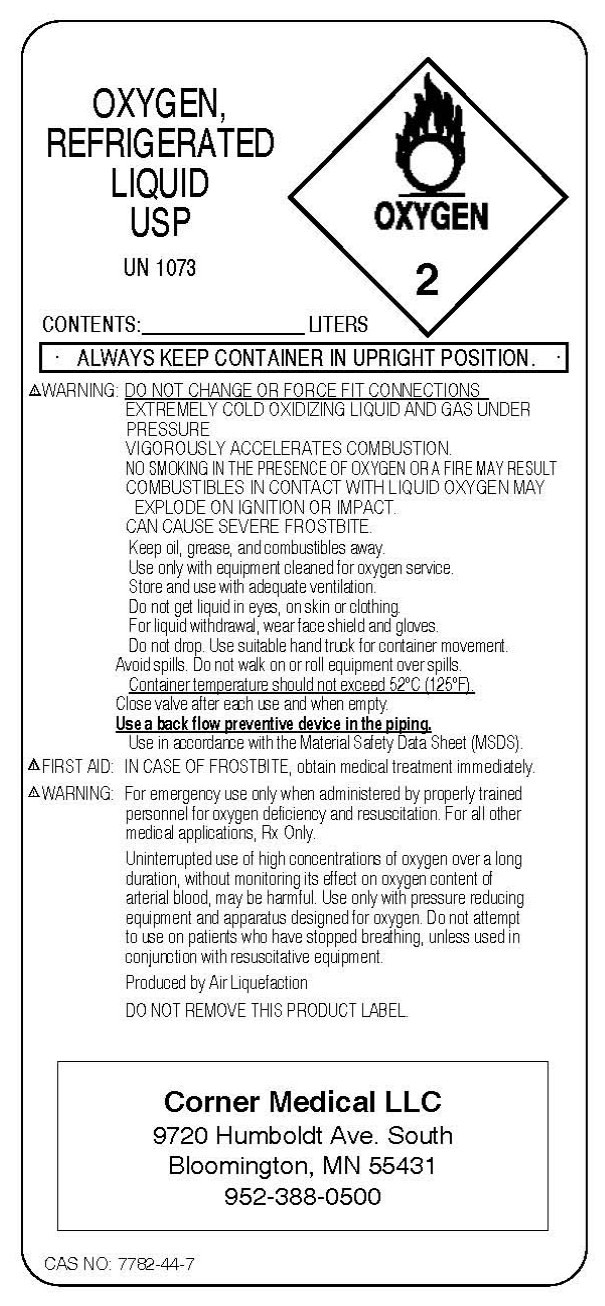 DRUG LABEL: Oxygen
NDC: 26482-0001 | Form: GAS
Manufacturer: Corner Medical 
Category: prescription | Type: HUMAN PRESCRIPTION DRUG LABEL
Date: 20091118

ACTIVE INGREDIENTS: Oxygen 99 L/100 L

Oxygen